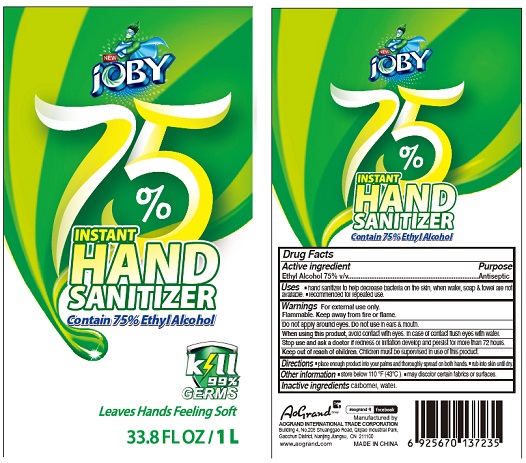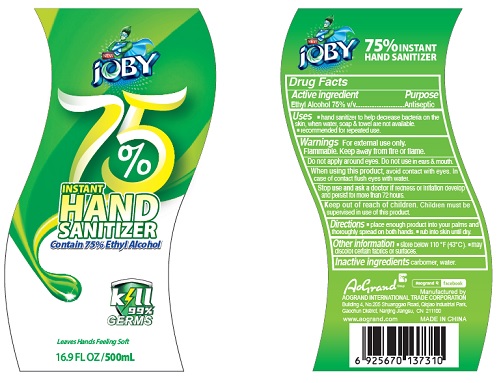 DRUG LABEL: Joby instant hand sanitrizer
NDC: 74621-026 | Form: GEL
Manufacturer: AOGRAND INTERNATIONAL TRADE CORPORATION
Category: otc | Type: HUMAN OTC DRUG LABEL
Date: 20200515

ACTIVE INGREDIENTS: ALCOHOL 75 mL/100 mL
INACTIVE INGREDIENTS: CARBOMER HOMOPOLYMER, UNSPECIFIED TYPE; WATER

Active Ingredient

Ethyl Alcohol 75% v/v.

Purpose

Antiseptic

Uses

- hand sanitizer to help decrease bacteria on the skin, when water, soap & towel are not available.
- recommended for repeated use.

Warnings

For external use only. Flammable. Keep away from heat or flame

Do not apply around eyes. Do not use in ears & mouth.

When using this product, avoid contact with eyes. In case of contact flush eyes with water.

Stop use and ask a doctor if redness or irritation develop and persist for more than 72 hours.

Keep out of reach of children. Children must be supervised in use of this product.

Directions

- place enough product into your palms and thoroughly spread on both hands.
- rub into skin until dry.

Other information

store below 110 ℉ (43 ℃).

may discolor certain fabrics or surfaces.

Inactive ingredients

carbomer, water.

Package Label - Principal Display Panel

Label 500 mL

Label 1000 mL